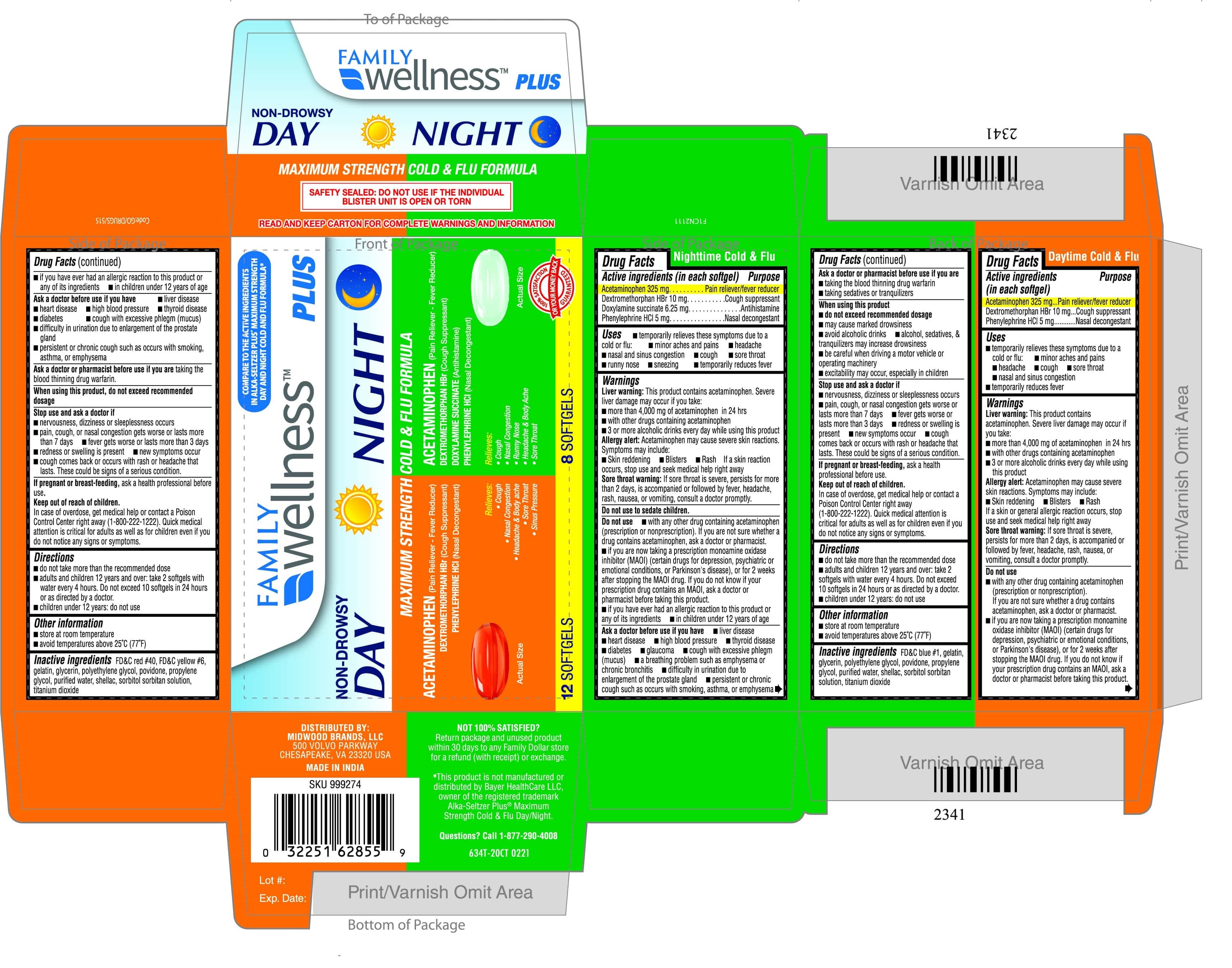 DRUG LABEL: MAXIMUM STRENGTH DAY-NIGHT COLD AND FLU FORMULA
NDC: 55319-935 | Form: KIT | Route: ORAL
Manufacturer: FAMILY DOLLAR
Category: otc | Type: HUMAN OTC DRUG LABEL
Date: 20250215

ACTIVE INGREDIENTS: ACETAMINOPHEN 325 mg/1 1; PHENYLEPHRINE HYDROCHLORIDE 5 mg/1 1; DEXTROMETHORPHAN HYDROBROMIDE 10 mg/1 1; DEXTROMETHORPHAN HYDROBROMIDE 10 mg/1 1; PHENYLEPHRINE HYDROCHLORIDE 5 mg/1 1; ACETAMINOPHEN 325 mg/1 1; DOXYLAMINE SUCCINATE 6.25 mg/1 1
INACTIVE INGREDIENTS: SHELLAC; TITANIUM DIOXIDE; FD&C YELLOW NO. 6; FD&C RED NO. 40; PROPYLENE GLYCOL; WATER; SORBITOL; POLYETHYLENE GLYCOL, UNSPECIFIED; POVIDONE; GELATIN; GLYCERIN; SORBITOL; TITANIUM DIOXIDE; FD&C BLUE NO. 1; POLYETHYLENE GLYCOL, UNSPECIFIED; POVIDONE; PROPYLENE GLYCOL; GELATIN; GLYCERIN; WATER; SHELLAC

634T - FAMILY DOLLAR DAY-NIGHT MAXIMUM STRENGTH COLD AND FLU 55319-935

DRUG FACTS - DAY MAXIMUM STRENGTH COLD AND FLU (633T)

DAY MAXIMUM STRENGTH COLD AND FLU

Active ingredients (in each SOFTGEL)

Acetaminophen 325 mg

Dextromethorphan hydrobromide 10 mg

Phenylephrine hydrochloride 5 mg

Purposes:

- Pain reliever/fever reducer
- Cough suppressant
- Nasal decongestant

INDICATIONS AND USAGE

Pain Reliever-Fever Reducer

Cough Suppressant

Antihistamine

Nasal Decongestant

- Nasal Congestion
- Headache & Body Ache
- Cough
- Runny Nose
- Sore Throat

Warnings

Liver warning: This product contains acetaminophen. Severe liver damage may occur if you take

· more than 4,000 mg of acetaminophen in 24 hours

· with other drugs containing acetaminophen

· 3 or more alcoholic drinks every day while using this product

Allergy alert: Acetaminophen may cause severe skin or severe

allergic reactions. Symptoms may include:

· skin reddening · blisters · rash · hives

· facial swelling · asthma (wheezing) · shock

If a skin or general allergic reaction occurs, stop use and seek medical help right away.

Sore throat warning: If sore throat is severe, persists for more than

2 days, is accompanied or followed by fever, headache, rash, nausea,

or vomiting, consult a doctor promptly.

Directions

· do not take more than the recommended dose

· adults and children 12 years and over: take 2 capsules with water

every 4 hours. Do not exceed 10 capsules in 24 hours or as

directed by a doctor.

· children under 12 years: do not use

INACTIVE INGREDIENT

Inactive ingredients: FD&C red #40, FD&C yellow #6, gelatin, glycerin, polyethylene glycol, povidone, propylene glycol, purified water, shellac, sorbitol sorbitan solution, titanium dioxide

Keep out of reach of children. In case of overdose, get medical help or contact a Poison Control Center right away(1 800-222-1222) Quick medical attention is critical for adults as well as for children even if you do not notice any signs or symptoms.

DRUG FACTS - NIGHT MAXIMUM STRENGTH COLD AND FLU

NIGHT MAXIMUM STRENGTH COLD AND FLU

Active ingredeints in each softgel

ACETAMINOPHEN 325 mg

Dextromethorphan Hydrobromide 10 mg

Doxylamine Succinate 6.25 mg

Phenylephrine HCl 5 mg

INACTIVE INGREDIENT

Inactive ingredients: FD&C Blue #1,gelatin, glycerin, polyethylene glycol, povidone, propylene glycol, purified water, shellac, , sorbitol sorbitan solution, titanium dioxide

PURPOSE

Pain Reliever-Fever Reducer

Cough Suppressant

Antihistamine

/Nasal Decongestant

Uses

· temporarily relieves these symptoms due to a cold or flu:

· minor aches and pains · headache · cough

· sore throat · nasal and sinus congestion

· temporarily reduces fever

Warnings

Liver warning: This product contains acetaminophen. Severe liver damage may occur if you take

· more than 4,000 mg of acetaminophen in 24 hours

· with other drugs containing acetaminophen

· 3 or more aloholic drinks every day while using this product

l Allergy alert: Acetaminophen may cause severe skin or severe

allergic reactions. Symptoms may include:

· skin reddening · blisters · rash · hives

· facial swelling · asthma (wheezing) · shock

If a skin or general allergic reaction occurs, stop use and seek medical help right away.

Sore throat warning: If sore throat is severe, persists for more than

2 days, is accompanied or followed by fever, headache, rash, nausea,

or vomiting, consult a doctor promptly.

Directions

· do not take more than the recommended dose

· adults and children 12 years and over: take 2 capsules with water

every 4 hours. Do not exceed 10 capsules in 24 hours or as

directed by a doctor.

· children under 12 years: do not use

Keep out of reach of children. In case of overdose, get medical help or contact a Poison Control Center right away. Quick medical attention is critical for adults as well as for children even if you do not notice any signs or symptoms.